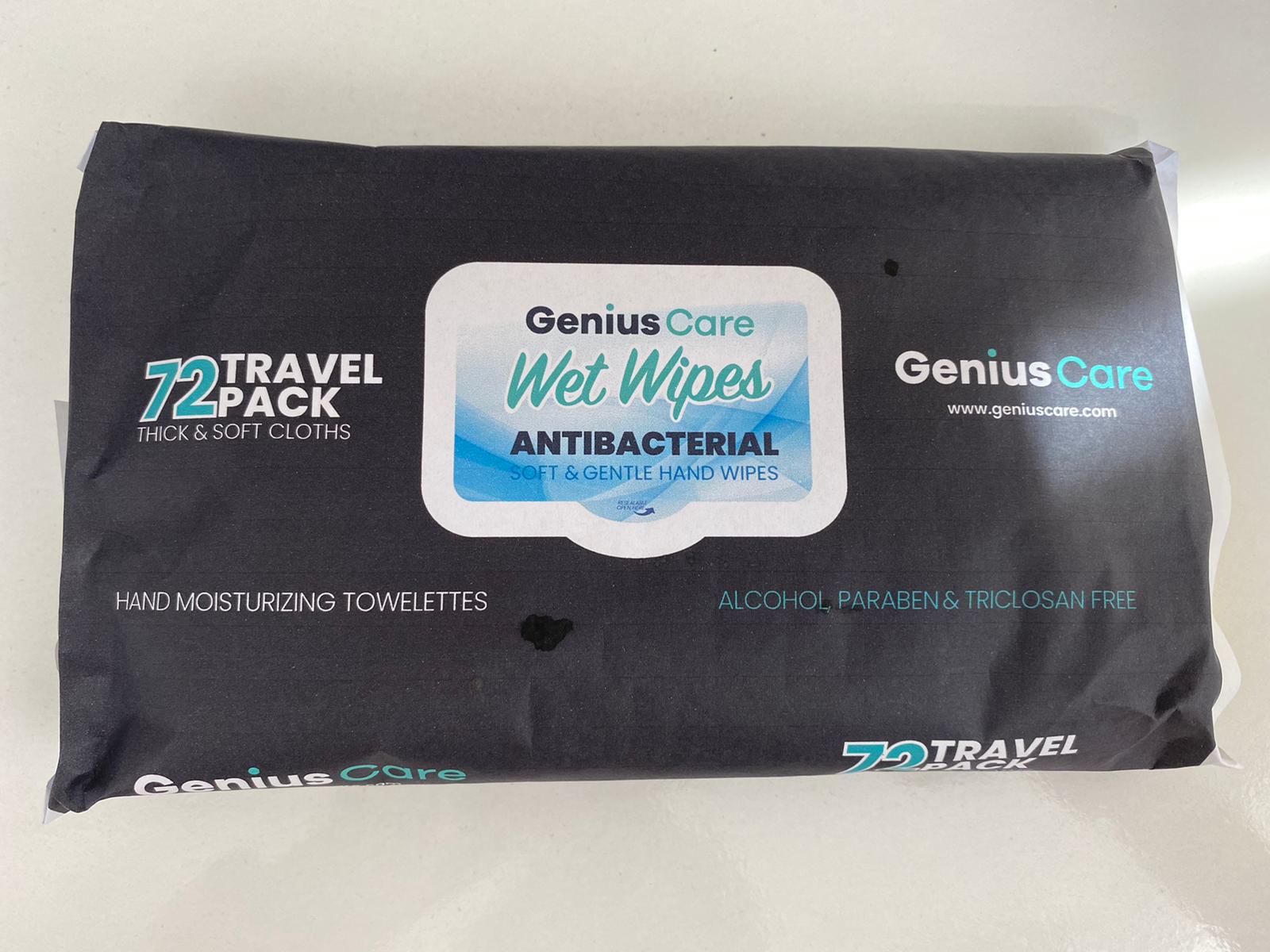 DRUG LABEL: GeniusCare Antibacterial Wet Wipes
NDC: 79320-123 | Form: CLOTH
Manufacturer: RK KOZMETIK VE HIJYEN URUNLERI SANAYI DIS TICARET ANONIM SIRKETI
Category: otc | Type: HUMAN OTC DRUG LABEL
Date: 20201013

ACTIVE INGREDIENTS: BENZALKONIUM CHLORIDE 0.1 mg/100 mL
INACTIVE INGREDIENTS: CHLORHEXIDINE 0.05 mg/100 mL; ANHYDROUS CITRIC ACID 0.02 mg/100 mL; PHENOXYETHANOL 0.8 mg/100 mL; PROPYLENE GLYCOL 0.5 mg/100 mL; WATER 97.18 mg/100 mL; COCAMIDOPROPYL BETAINE 0.5 mg/100 mL; PEG-7 GLYCERYL COCOATE 0.3 mg/100 mL; BENZOIC ACID 0.1 mg/100 mL; DEHYDROACETIC ACID 0.1 mg/100 mL; POLYOXYL 40 HYDROGENATED CASTOR OIL 0.3 mg/100 mL; EDETATE SODIUM 0.02 mg/100 mL

ANTIBACTERIAL WET WIPES

Perfect for quick clean-ups when soap and water are not available.

Genius Care Wet Wipes ANTIBACTERIAL SOFT GENTLE HAND WIPES

REDUCES 99.0% OF BACTERIA*

72 TRAVEL PACK THICK & SOFT CLOTHS

ALCOHOL, PARABEN & TRICLOSAN FREE

ANTIBACTERIAL WET WIPES

Travel Pack is convenient to carry for use anytime, anywhere.

*Reduces 99.9% of bacterial and fungal strains as tested in a laboratory setting (Staphylococcus aureus)

(Pseudomonas aeruginosa)(Escherichia coli)(Enterococcus hirae)(Candida albicans)

Active Ingredient(s)

Benzalkonium chloride 0.1 %. Purpose: Antiseptic

Purpose

Antiseptic, GeniusCare

Genius Care Wet Wipes ANTIBACTERIAL SOFT GENTLE HAND WIPES

Uses

To Dispense Wipe: Peel back front label slowly. Remove wipes.

To Reseal Pouch: Firmly run thumb over the label.

Do not Flush

Warnings

For external use only.

Do not use if you are allergic to any of the ingredients

When using this product, do not get into eyes. If contact occurs, rinse thoroughly with water.

Stop use and ask a doctor if irritation or rash develops and continues for more than 72 hours.

Keep out of reach of children. If swallowed, get medical help or contact a Poison Control Center right away.

Ask a doctor before use

When using this product avoid contact with eyes. If contact occurs, rinse thoroughly with water.

Stop use and ask a doctor if irritation or rash develops and continues for more than 72 hours.

Keep out of reach of children. If swallowed, get medical help or contact a Poison Control Center right away.

Directions

For use by adults and children 2 years and over

Use decreases bacteria on skin.

Apply to hands
Allow to dry without wiping

Other information

DO NOT FLUSH

Inactive ingredients

Water, Propylene Glycol, Cocamidopropyl Betain, PEG-7 Glyceryl Cocoate, Phenoxyethanol, Benzoic Acid, Dehydroxyacetic Acid, Fragrance, PEG-40 Hdrogenated Castor Oil, Tetrasodium EDTA, Chlorhexidin Digluconat, Citric Acid.

Package Label - Principal Display Panel

NDC: 79320-123-01